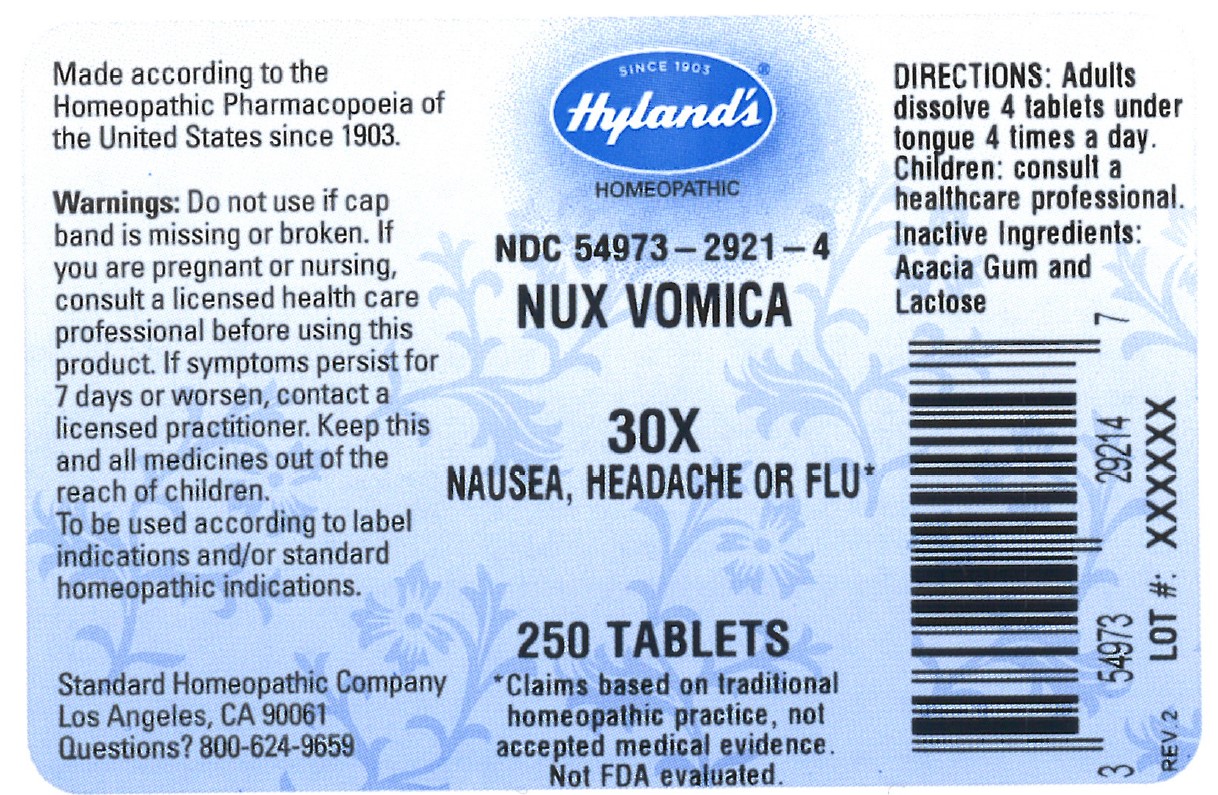 DRUG LABEL: NUX VOMICA
NDC: 54973-2921 | Form: TABLET
Manufacturer: Hyland's Inc.
Category: homeopathic | Type: HUMAN OTC DRUG LABEL
Date: 20221220

ACTIVE INGREDIENTS: STRYCHNOS NUX-VOMICA SEED 30 [hp_X]/1 1
INACTIVE INGREDIENTS: ACACIA; LACTOSE

NUX VOMICA 30X

ACTIVE INGREDIENT

NUX VOMICA 30X

PURPOSE

NAUSEA, HEADACHE OR FLU

INDICATIONS AND USAGE

NAUSEA, HEADACHE OR FLU

Warnings

Do not use if cap band is missing or broken.

PREGNANCY OR BREAST FEEDING

If you are pregnant or nursing, consult a licensed health care professional before using this product.

ASK DOCTOR

If symptoms persist for 7 days or worsen, contact a licensed practitioner.

KEEP OUT OF REACH OF CHILDREN

Keep this and all medicines out of the reach of children.

WHEN USING

To be used according to label indications and/or standard homeopathic indications.

Directions

Adults: Dissolve 4 tablets under tongue 4 times a day.

Children: consult a healthcare professional.

Inactive Ingredients

Acacia Gum and Lactose

Questions?

800-624-9659

Dosage and Administration (Directions)

Adults: Dissolve 4 tablets under tongue 4 times a day.

Children: consult a healthcare professional.

PRINCIPAL DISPLAY PANEL - 250 Tablet Bottle Label

SINCE 1903
Hyland's ®
HOMEOPATHIC

NDC 54973-2921-4

NUX VOMICA

30X

NAUSEA, HEADACHE OR

FLU *

250 TABLETS

*Claims are based on traditional

homeopathic practice, not

accepted medical evidence.

Not FDA evaluated.